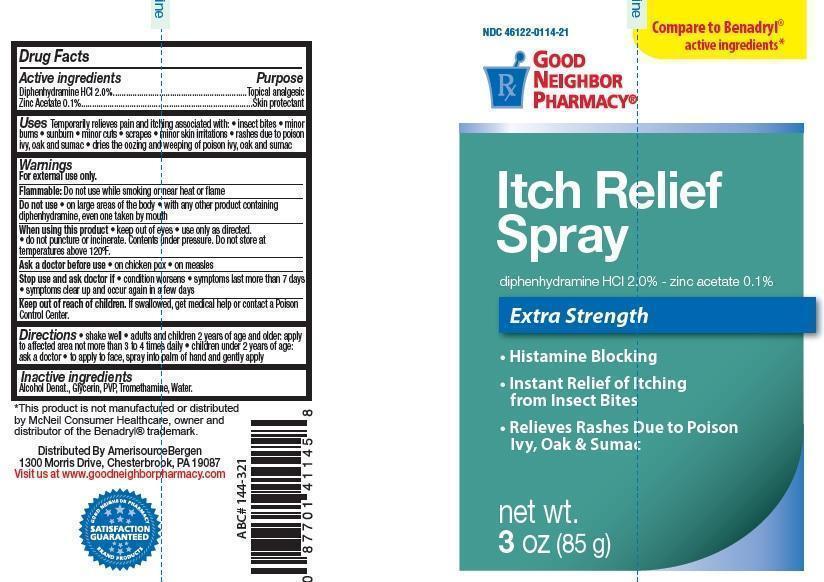 DRUG LABEL: Good Neighbor Pharmacy Itch Relief
NDC: 46122-114 | Form: AEROSOL, SPRAY
Manufacturer: AmerisourceBergen Drug Corporation
Category: otc | Type: HUMAN OTC DRUG LABEL
Date: 20150908

ACTIVE INGREDIENTS: DIPHENHYDRAMINE HYDROCHLORIDE 2 g/100 g; Zinc Acetate 0.1 g/100 g
INACTIVE INGREDIENTS: ALCOHOL; GLYCERIN; PVP/VA COPOLYMER; TROMETHAMINE; WATER

Good Neighbor Pharmacy Itch Relief

Active ingredients

- Diphenhydramine HCI 2.0%
- Zinc Acetate 0.1%

Purpose

- Topical analgesic
- Skin protectant

Uses

Temporarily relieves pain and itching associated with: • insect bites • minor

burns • sunburn • minor cuts • scrapes • minor skin irritations • rashes due to poison

ivy, oak and sumac • dries the oozing and weeping of poison ivy, oak and sumac

Warnings

For external use only.

Flammable:

Do not use while smoking or near heat or flame

Do not use

on large areas of the body • with any other product containing diphenhydramine, even one taken by mouth

When using this product

• keep out of eyes • use only as directed.

• do not puncture or incinerate. Contents under pressure. Do not store at temperatures above 120ºF.

Ask a doctor before use

• on chicken pox • on measles

Stop use and ask doctor if

• condition worsens • symptoms last more than 7 days

• symptoms clear up and occur again in a few days

Keep out of reach of children.

If swallowed, get medical help or contact a Poison Control Center.

Directions

• shake well • adults and children 2 years of age and older: apply to affected area not more than 3 to 4 times daily • children under 2 years of age: ask a doctor • to apply to face, spray into palm of hand and gently apply

Inactive ingredients

Alcohol Denat., Glycerin, PVP, Tromethamine, Water.

*This product is not manufactured or distributed

by McNeil Consumer Healthcare, owner and

distributor of the Benadryl® trademark.

Distributed By AmerisourceBergen

1300 Morris Drive, Chesterbrook, PA 19087

Visit us at www.goodneighborpharmacy.com